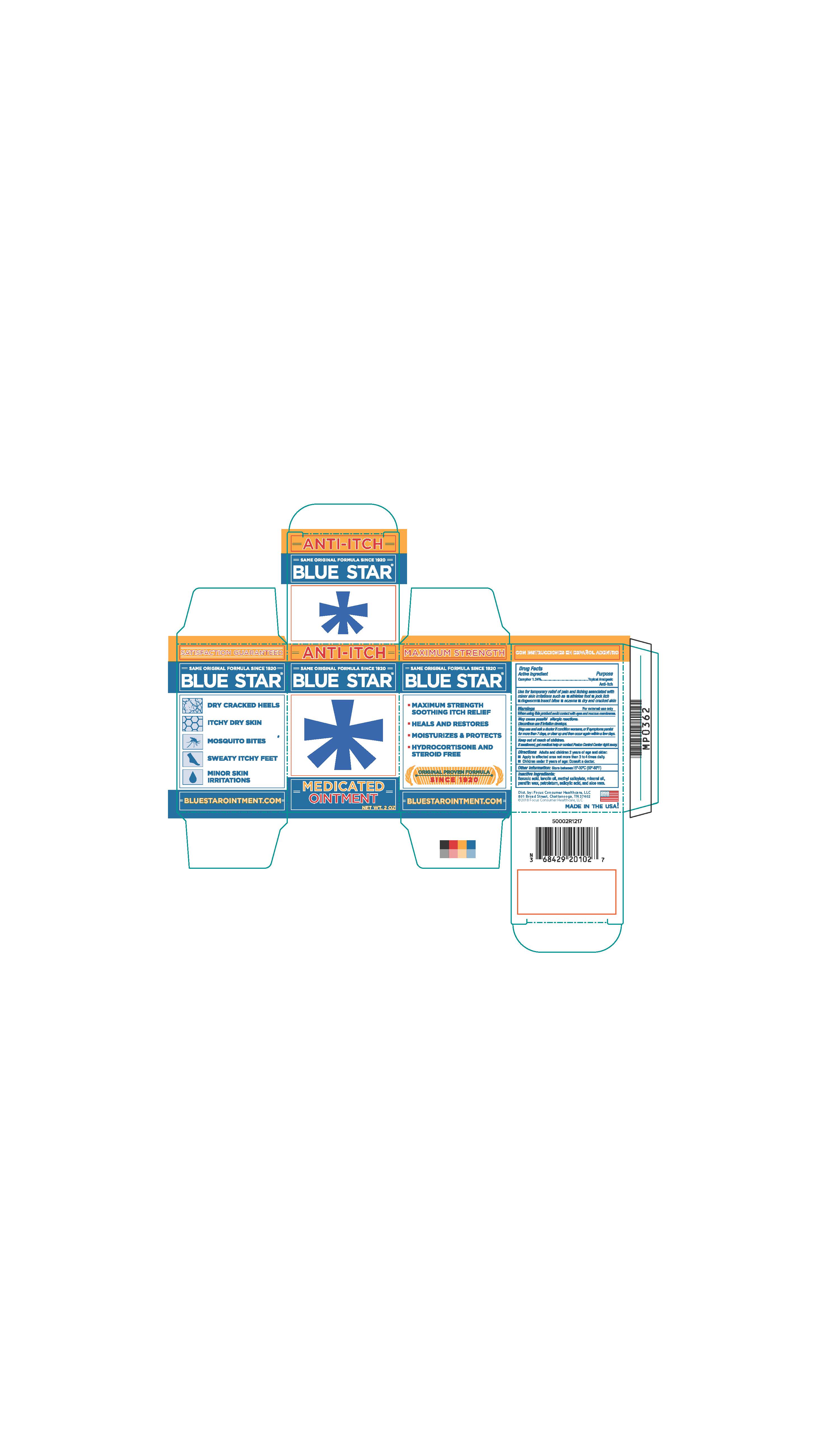 DRUG LABEL: Blue Star Medicated
NDC: 71687-2010 | Form: OINTMENT
Manufacturer: Focus Consumer Healthcare, LLC
Category: otc | Type: HUMAN OTC DRUG LABEL
Date: 20250414

ACTIVE INGREDIENTS: CAMPHOR (SYNTHETIC) 1.24 g/100 g
INACTIVE INGREDIENTS: LANOLIN OIL; METHYL SALICYLATE; MINERAL OIL; PETROLATUM; SALICYLIC ACID; PARAFFIN; ALOE VERA LEAF; BENZOIC ACID

Blue Star

Active Ingredient

Camphor 1.24%

Purpose

Toplcal Analgesic, Anti-itch

INDICATIONS AND USAGE

Use for temporarily relief of pain and itching associated with minor skin irritations.

Warnings

For external use only

When using this product avoid contact with eyes

Stop use and ask a doctor if condition worsens, or if symptoms persist for more than 7 days, or clear up and occur again with a few days

Keep out of reach of children

If swallowed, get medical help or contact: Poison Control Center right away

DOSAGE AND ADMINISTRATION

- Adults and children 2 years of age and older. Apply to affected area not more than 3 to 4 times daily
- Children under 2 years of age; Consult a doctor

INACTIVE INGREDIENT

Benzoic acid, lanolin oil, methyl salicylate, mineral oil, parafin wax, petrolatum, salicylic acid, aloe oil extract